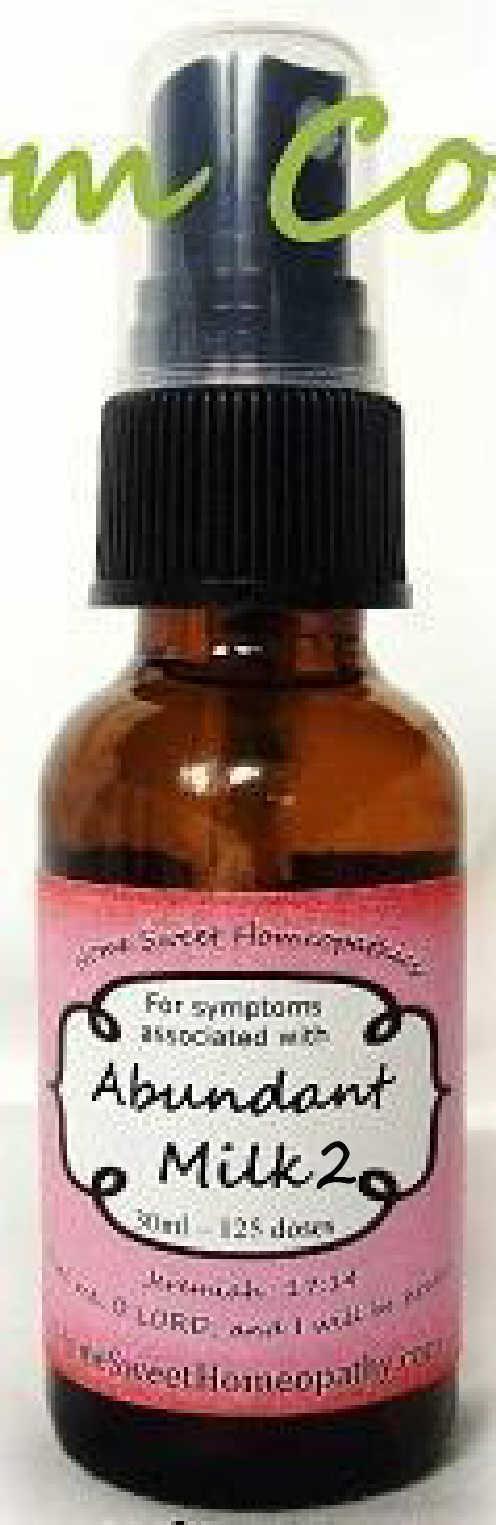 DRUG LABEL: Abundant Milk 2
NDC: 59667-0003 | Form: SPRAY
Manufacturer: Home Sweet Homeopathics
Category: homeopathic | Type: HUMAN OTC DRUG LABEL
Date: 20130815

ACTIVE INGREDIENTS: ATROPA BELLADONNA 30 [hp_C]/30 [hp_C]; BRYONIA ALBA ROOT 30 [hp_C]/30 [hp_C]; CHELIDONIUM MAJUS 30 [hp_C]/30 [hp_C]; CINCHONA OFFICINALIS BARK 30 [hp_C]/30 [hp_C]; ARABICA COFFEE BEAN 30 [hp_C]/30 [hp_C]; STRYCHNOS IGNATII SEED 30 [hp_C]/30 [hp_C]; FORMALDEHYDE 30 [hp_C]/30 [hp_C]; SKIM MILK 30 [hp_C]/30 [hp_C]; COW MILK FAT 30 [hp_C]/30 [hp_C]; EGG PHOSPHOLIPIDS 30 [hp_C]/30 [hp_C]; PHOSPHORUS 30 [hp_C]/30 [hp_C]; PHYTOLACCA AMERICANA ROOT 30 [hp_C]/30 [hp_C]; CLAVICEPS PURPUREA SCLEROTIUM 30 [hp_C]/30 [hp_C]
INACTIVE INGREDIENTS: WATER; ALCOHOL

PURPOSE

To help increase milk supply.

To be used according to label indications.

Active Ingredients:

Belladonna, Bryonia, Chelidonium, Cinchona Officionalis, Coffea Cruda, Ignatia, Formalinum, Lac Defloratum, Lac Vaccini Flos, Lecithinum, Phosphorus, Phytolacca, Secale

Directions:

Spritz 1 time under the tongue 3 x per day until improvement is seen, then dose 1x per day for 3 days. Dose when symptoms return.

Keep out of reach of children.

WARNINGS

If no improvement is seen after 7 days or new symptoms develop, discontinue use.

Inactive Ingredients:

In reverse osmosis water with less than 1% alcohol. May contain trace amounts of lactose.